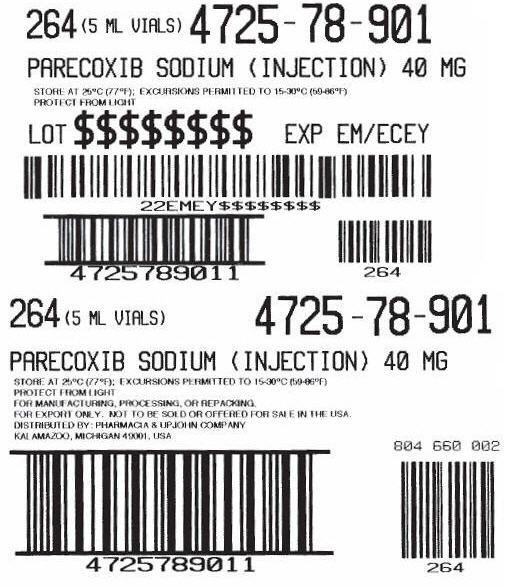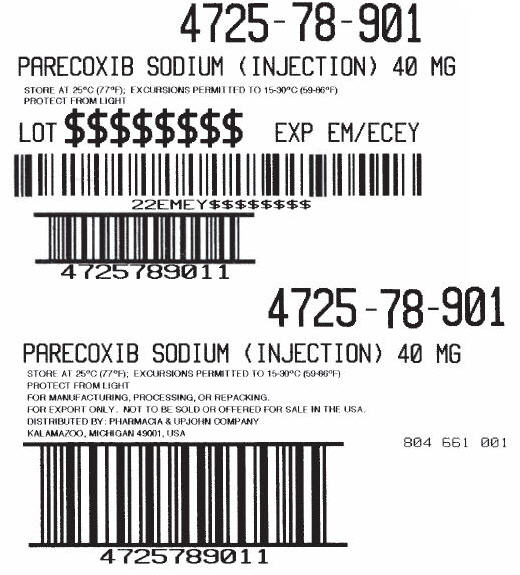 DRUG LABEL: Parecoxib Sodium
NDC: 0009-0048 | Form: INJECTION, POWDER, FOR SOLUTION
Manufacturer: Pharmacia & Upjohn Company LLC
Category: prescription | Type: HUMAN PRESCRIPTION DRUG LABEL
Date: 20250917

ACTIVE INGREDIENTS: PARECOXIB SODIUM 40 mg/1 1
INACTIVE INGREDIENTS: SODIUM PHOSPHATE, DIBASIC, ANHYDROUS; PHOSPHORIC ACID; SODIUM HYDROXIDE; WATER

PARECOXIB SODIUM (INJECTION) 40 MG

PRINCIPAL DISPLAY PANEL - Shipping Label

264 (5 ML VIALS) 4725-78-901

PARECOXIB SODIUM (INJECTION) 40 MG

STORE AT 25°C (77°F); EXCURSIONS PERMITTED TO 15-30°C (59-86°F)
PROTECT FROM LIGHT

LOT $$$$$$$$ EXP EM/ECEY

264 (5 ML VIALS)
4725-78-901

PARECOXIB SODIUM (INJECTION) 40 MG

STORE AT 25°C (77°F); EXCURSIONS PERMITTED TO 15-30°C (59-86°F)
PROTECT FROM LIGHT
FOR MANUFACTURING, PROCESSING, OR REPACKING.
FOR EXPORT ONLY. NOT TO BE SOLD OR OFFERED FOR SALE IN THE USA.
DISTRIBUTED BY: PHARMACIA & UPJOHN COMPANY
KALAMAZOO, MICHIGAN 49001, USA

804 660 002

PRINCIPAL DISPLAY PANEL - Shipping Label - Pallet

4725-78-901

PARECOXIB SODIUM (INJECTION) 40 MG

STORE AT 25°C (77°F); EXCURSIONS PERMIITTED TO 15-30°C (59-86°F)
PROTECT FROM LIGHT

LOT $$$$$$$$ EXP EM/ECEY

4725-78-901

PARECOXIB SODIUM (INJECTION) 40 MG

STORE AT 25°C (77°F); EXCURSIONS PERMITTED TO 15-30°C (59-86°F)
PROTECT FROM LIGHT
FOR MANUFACTURING, PROCESSING, OR REPACKING.
FOR EXPORT ONLY. NOT TO BE SOLD OR OFFERED FOR SALE IN THE USA.
DISTRIBUTED BY: PHARMACIA & UPJOHN COMPANY
KALAMAZOO, MICHIGAN 49001, USA

804 661 001